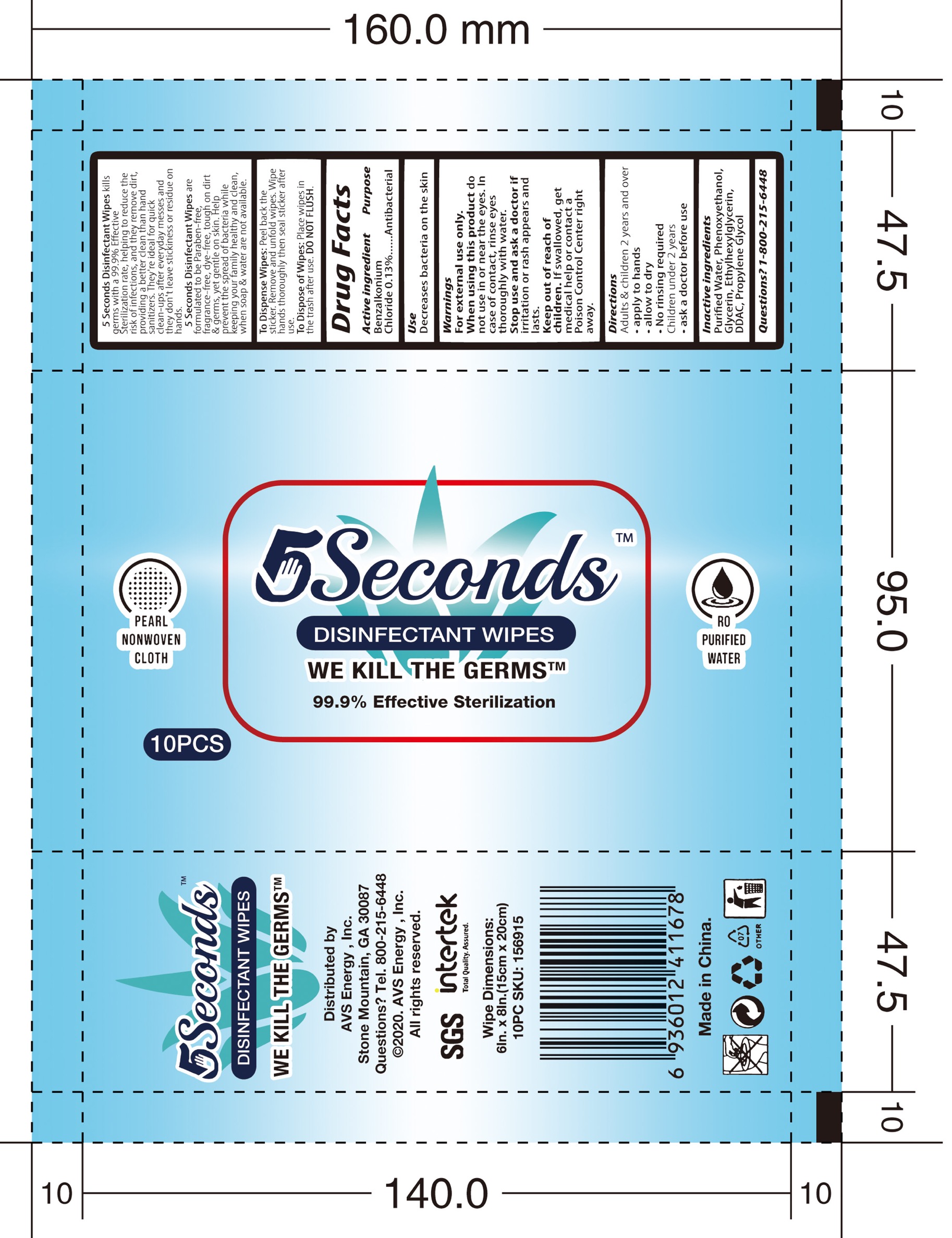 DRUG LABEL: 5Seconds Disinfectant Wipes
NDC: 77871-003 | Form: SOLUTION
Manufacturer: AVS Energy Inc
Category: otc | Type: HUMAN OTC DRUG LABEL
Date: 20200713

ACTIVE INGREDIENTS: BENZALKONIUM CHLORIDE 7.8 mg/1 1
INACTIVE INGREDIENTS: WATER; GLYCERIN; PHENOXYETHANOL; ETHYLHEXYLGLYCERIN; PROPYLENE GLYCOL

Active Ingredient(s)

Benzalkonium Chloride: 0.13%

Purpose

Antibacterial

Use

Decrease bacteria on the skin

Warnings

For external use only.

When using this product, do not use in or near the eyes. In case of contact, rinse eyes thoroughly with water

Stop use and ask a doctor if irritation or rash appears and lasts

Keep out of reach of children. If swallowed, get medical help or contact a Poison Control Center right away.

Directions

Adults and children 2 years and over:

- Apply to hands
- Allow to dry
- No rinsing reqired

Children under 2 years

- Ask a doctir before use

Inactive ingredients

Water, Phenoxyehtanol, Glycerin, Ethylhexylglycerin, DDAC, Propylene Glycol